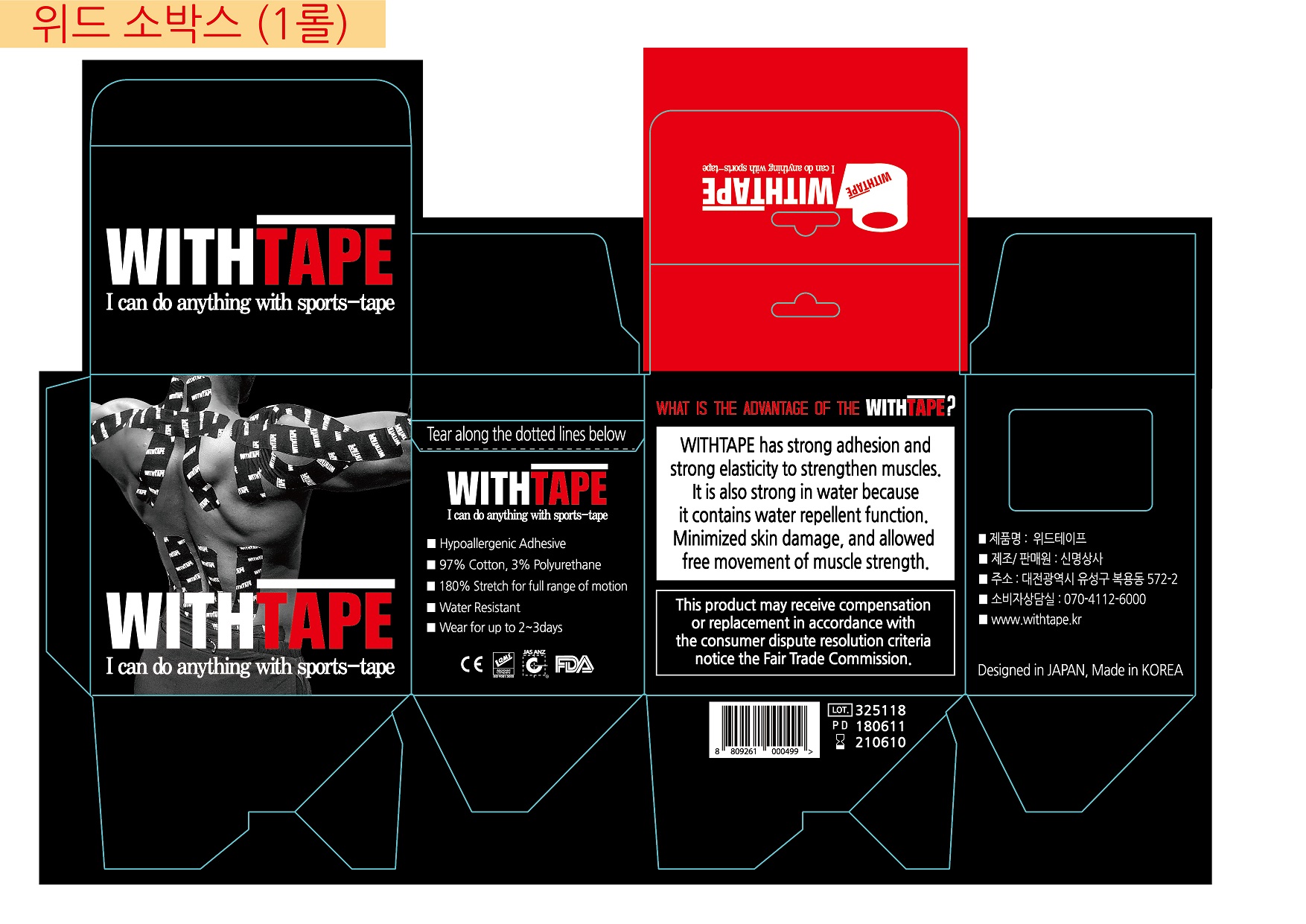 DRUG LABEL: WITHTAPE
NDC: 55692-300 | Form: TAPE
Manufacturer: Barox Co., Ltd.
Category: otc | Type: HUMAN OTC DRUG LABEL
Date: 20190321

ACTIVE INGREDIENTS: CAPSICUM ANNUUM WHOLE 0.05 g/100 g
INACTIVE INGREDIENTS: COTTON FIBER

Drug Facts

ACTIVE INGREDIENT

CAPSICUM ANNUUM extract

INACTIVE INGREDIENT

hidenol, cotton, paper

PURPOSE

to strengthen muscles

keep out of reach of the children

INDICATIONS AND USAGE

Cut the tape into scissors as long as you want to attach it according to the skeleton of your body, then cut the end edge round and attach it to the skin to prevent falling

WARNINGS

- for exeternal use only. Do not use for internal use
- avoid direct sunlight and store in cool and area of low humidity
- avoid placing the product near fire and store out in reach of children

DOSAGE AND ADMINISTRATION

for external use only